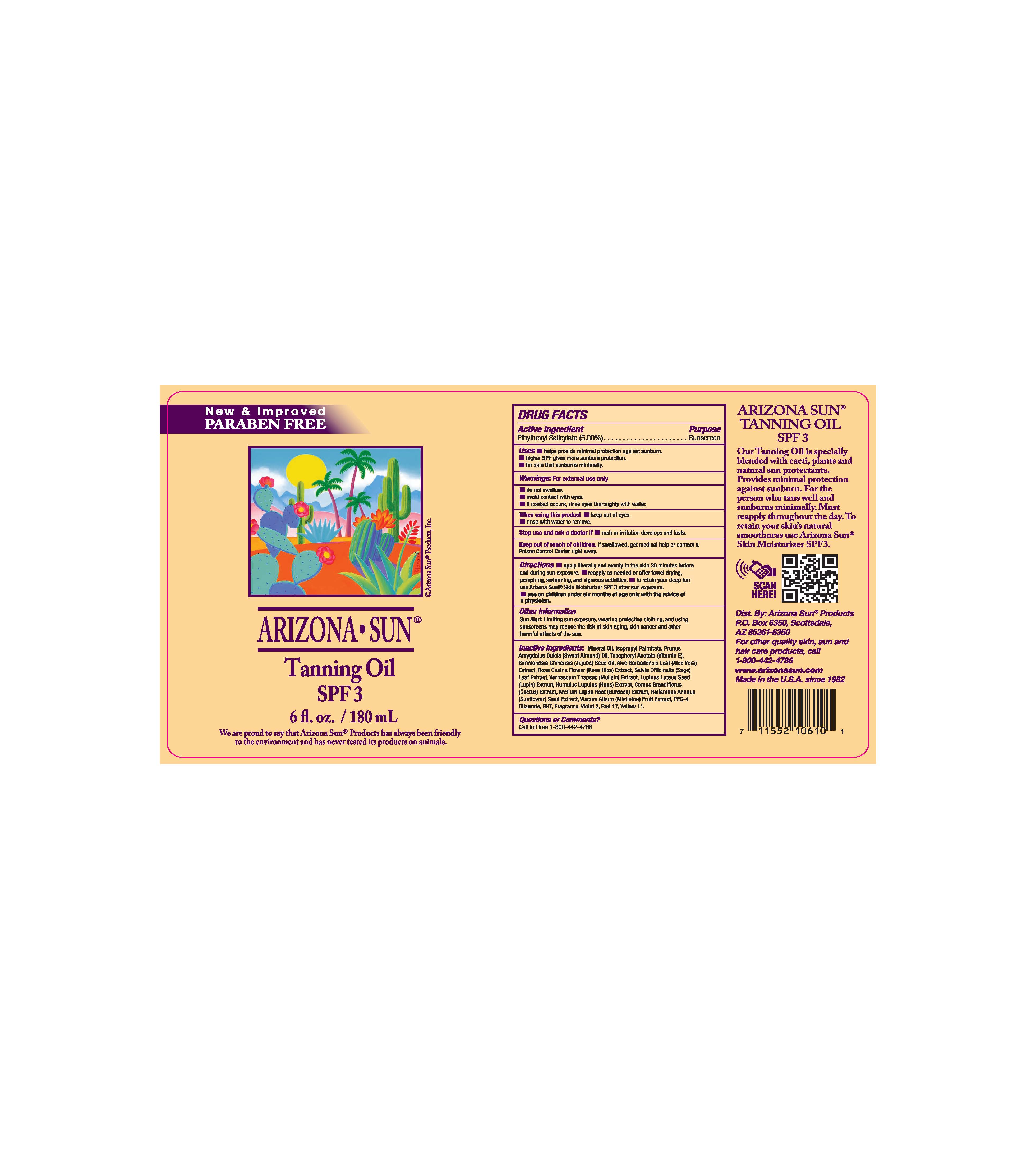 DRUG LABEL: Arizona Sun Tanning Oil SPF 3
NDC: 61973-200 | Form: OIL
Manufacturer: Arizona Sun Products
Category: otc | Type: HUMAN OTC DRUG LABEL
Date: 20240206

ACTIVE INGREDIENTS: OCTISALATE 50 mg/1 g
INACTIVE INGREDIENTS: ISOPROPYL PALMITATE; .ALPHA.-TOCOPHEROL ACETATE; SELENICEREUS GRANDIFLORUS FLOWER; HOPS; SAGE; ROSA CANINA FLOWER; D&C RED NO. 17; ARCTIUM LAPPA ROOT; MULLEIN LEAF; PEG-4 DILAURATE; SUNFLOWER SEED; D&C YELLOW NO. 11; MINERAL OIL; SIMMONDSIA CHINENSIS SEED; ALOE VERA LEAF; LUPINUS LUTEUS SEED; VISCUM ALBUM FRUIT; ALMOND OIL; BUTYLATED HYDROXYTOLUENE; D&C VIOLET NO. 2

Tanning Oil

Active Ingredients

Ethylhexyl Salicylate (5.00%)

Purpose

Sunscreen

Uses

Helps provide mimial protection agains sunburn. Higher SPF gives more sunburn protection. For skin that sunburns minimally.

Warnings

For external use only. Do not swallow. Avoid contact with the eyes. If contact occurs, rinse eyes thouroughly with water.

When using this product

keep out of eyes. Rinse with water to remove.

Keep out of the reach of children.

If swallowed get medical help or contact a poison control center right away.

Stop use and ask a doctor if

rash or irritation develops and lasts.

Directions

Apply liberally and evenly to the skin 30 minutes before and during sun exposure. Reapply as needed or after towel drying, perspiring, swimming, and vigorous activities. To retain your deep tan use Arizona Sun Moisturizer SPF 3 after sun exposure. Use on childeren under the age of 6 months of age only with the advise of a physician.

Other Information

Sun Alert: Limiting sun exposure, wearing protective clothing, and using suscreen may reduce the risk of skin aging, skin cancer and other harmful effects of the sun.

Inactive Ingredients

Mineral Oil, Isopropyl Palmitate, Prunus Amygdalus Dulcis (Sweet Almond) Oil, Tocopheryl Acetate (Vitamin E), Simmondsia Chinensis (Jojoba) Seed Oil, Aloe Barbadensis Leaf (Aloe Vera) Extract, Rosa Canina Flower (Rose Hips) Extract, Salvia Officinalis (Sage) Leaf Extract, Verbascum Thapsus (Mullein) Extract, Lupinus Luteus Seed (Lupin) Extract, Humulus Lupulus (Hops) Extract, Cereus Grandiflorus (Cactus) Extract, Arctium Lappa Root (Burdock) Extract, Helianthus Annuus (Sunflower) Seed Extract, Viscum Album (Mistletoe) Fruit Extract, PEG-4 Dilaurate, BHT, Fragrance, Violet 2, Red 17, Yellow 11.

Questions or Comments?

Call toll free 1-800-442-4786